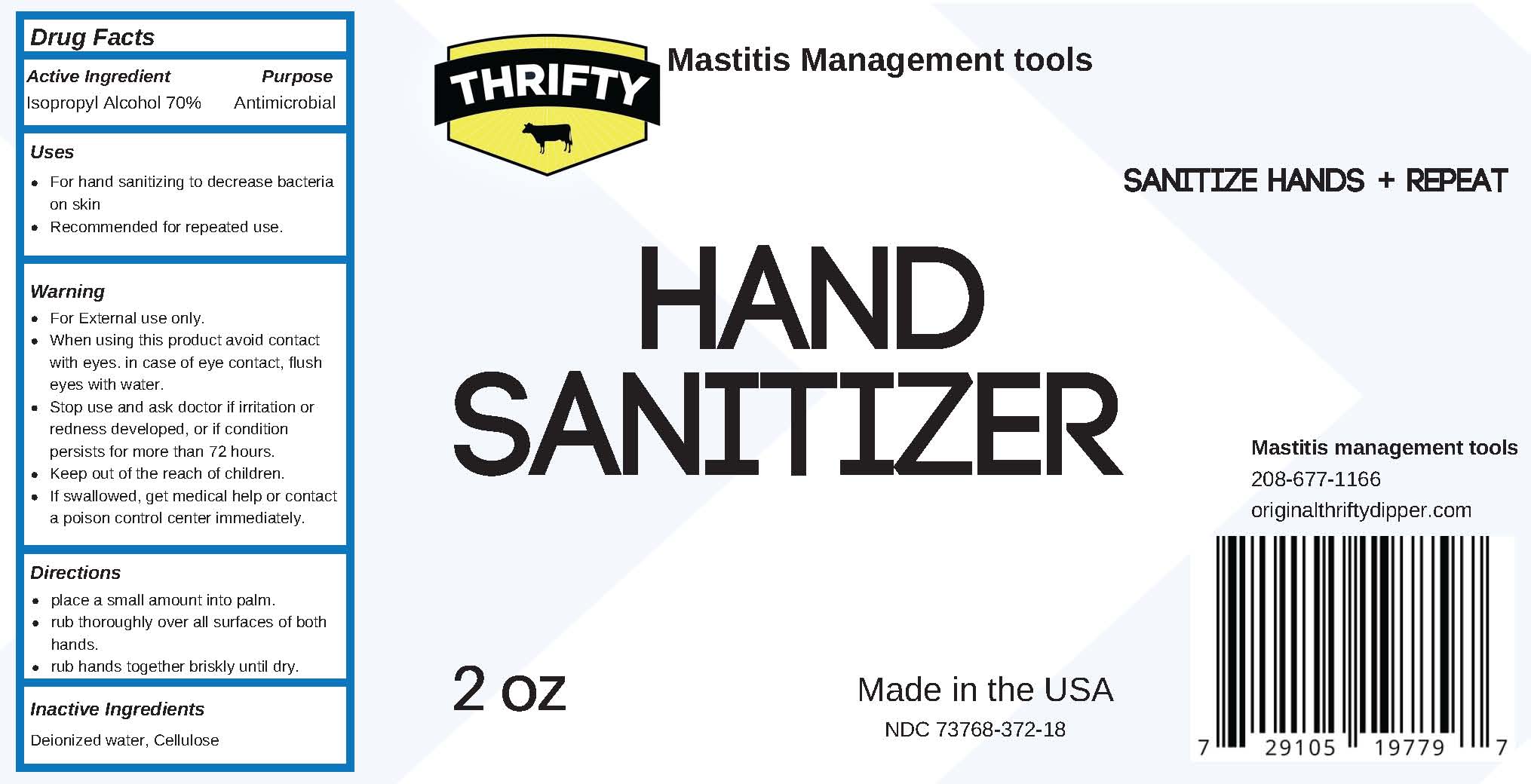 DRUG LABEL: Hand Sanitizer
NDC: 73768-372 | Form: GEL
Manufacturer: Mastitis Management Tools, Inc.
Category: otc | Type: HUMAN OTC DRUG LABEL
Date: 20201231

ACTIVE INGREDIENTS: ISOPROPYL ALCOHOL 0.7 L/1 L
INACTIVE INGREDIENTS: HYDROXYETHYL CELLULOSE (4000 MPA.S AT 1%); WATER

Active Ingredient

Isopropyl Alcohol 70%

Purpose

Antimicrobial

Uses

- For hand sanitizing to decrease bacteria on skin
- Recommended for repeated use

Warning

- For External use only.
- When using this product avoid contact with eyes. in case of eye contact, flush eyes with water.
- Stop use and ask doctor if irritation or redness developed, or if condition persists for more than 72 hours.
- Keep out of the reach of children.
- If swallowed, get medical help or contact a poison control center immediately.

Directions

- place a small amount into palm.
- rub thoroughly over all surfaces of both hands.
- rub hands together briskly until dry.

Inactive Ingredients

Deionized water, Cellulose